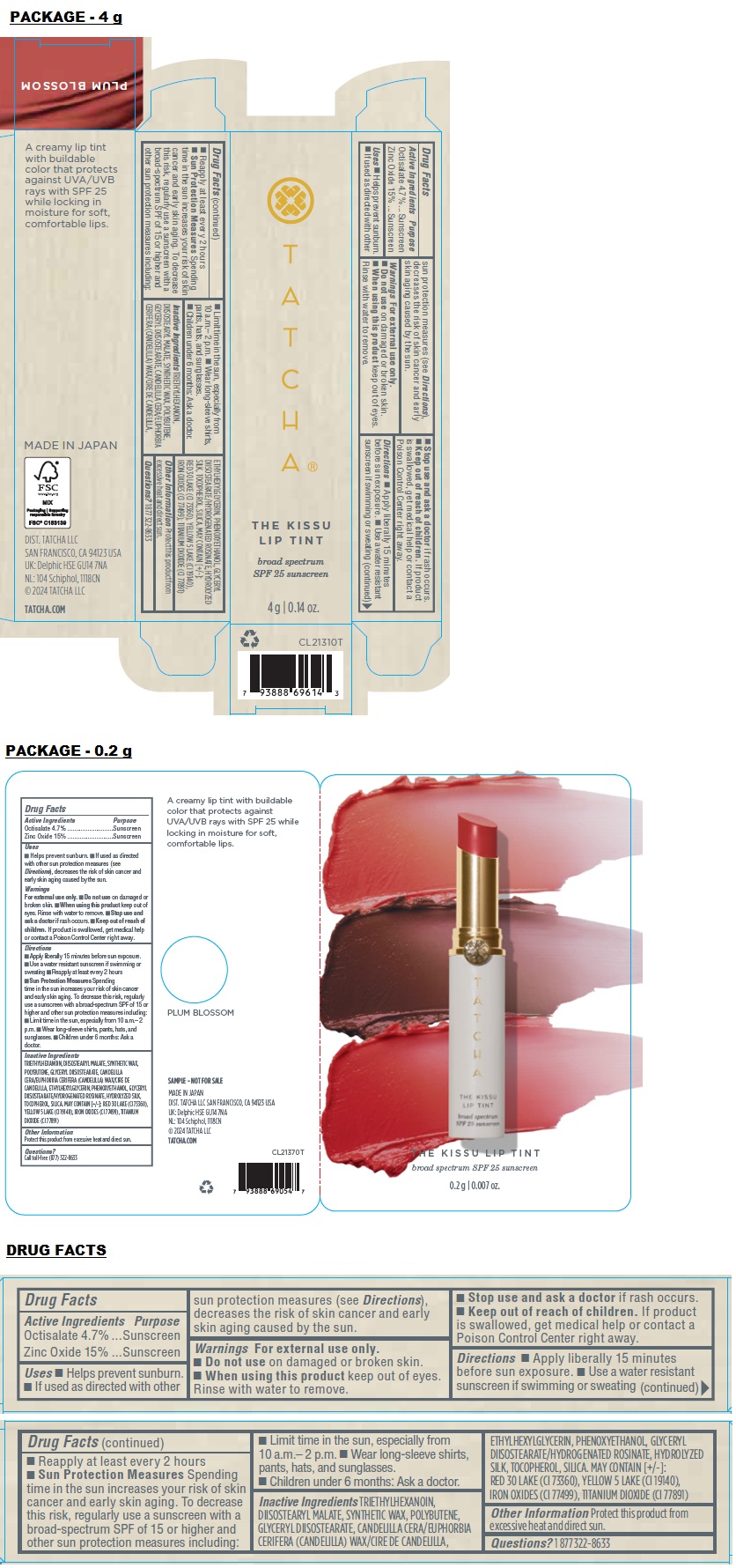 DRUG LABEL: TATCHA THE KISSU LIP TINT SPF 25 PLUM BLOSSOM
NDC: 69417-162 | Form: LIPSTICK
Manufacturer: TATCHA INC.
Category: otc | Type: HUMAN OTC DRUG LABEL
Date: 20240314

ACTIVE INGREDIENTS: OCTISALATE 4.7 g/100 g; ZINC OXIDE 15 g/100 g
INACTIVE INGREDIENTS: TRIETHYLHEXANOIN; DIISOSTEARYL MALATE; PARAFFIN; POLYBUTENE (1400 MW); GLYCERYL DIISOSTEARATE; CANDELILLA WAX; ETHYLHEXYLGLYCERIN; PHENOXYETHANOL; TOCOPHEROL; SILICON DIOXIDE; D&C RED NO. 30; FD&C YELLOW NO. 5 ALUMINUM LAKE; FERROSOFERRIC OXIDE; TITANIUM DIOXIDE

TATCHA® THE KISSU LIP TINT SPF 25 PLUM BLOSSOM

Active Ingredients

Octisalate 4.7%
Zinc Oxide 15%

Purpose

Sunscreen

Uses

• Helps prevent sunburn.
• If used as directed with other sun protection measures (see Directions), decreases the risk of skin cancer and early skin aging caused by the sun.

Warnings

For external use only.
• Do not use on damaged or broken skin.
• When using this product keep out of eyes. Rinse with water to remove.
• Stop use and ask a doctor if rash occurs.

• Keep out of reach of children. If product is swallowed, get medical help or contact a Poison Control Center right away.

Directions

• Apply liberally 15 minutes before sun exposure. • Use a water resistant sunscreen if swimming or sweating
• Reapply at least every 2 hours
• Sun Protection Measures Spending time in the sun increases your risk of skin cancer and early skin aging. To decrease this risk, regularly use a sunscreen with a broad-spectrum SPF of 15 or higher and other sun protection measures including:
• Limit time in the sun, especially from 10 a.m.– 2 p.m. • Wear long-sleeve shirts, pants, hats, and sunglasses.
• Children under 6 months: Ask a doctor.

Inactive Ingredients

TRIETHYLHEXANOIN, DIISOSTEARYL MALATE, SYNTHETIC WAX, POLYBUTENE, GLYCERYL DIISOSTEARATE, CANDELILLA CERA/EUPHORBIA CERIFERA (CANDELILLA) WAX/CIRE DE CANDELILLA, ETHYLHEXYLGLYCERIN, PHENOXYETHANOL, GLYCERYL DIISOSTEARATE/HYDROGENATED ROSINATE, HYDROLYZED SILK, TOCOPHEROL, SILICA. MAY CONTAIN [+/-]: RED 30 LAKE (CI 73360), YELLOW 5 LAKE (CI 19140), IRON OXIDES (CI 77499), TITANIUM DIOXIDE (CI 77891)

Other Information

Protect this product from excessive heat and direct sun.

Questions?

1 877 322-8633

broad spectrum SPF 25 sunscreen

A creamy lip tint with buildable color that protects against UVA/UVB rays with SPF 25 while locking in moisture for soft, comfortable lips.

SAMPLE- NOT FOR SALE

MADE IN JAPAN

DIST. TATCHA LLC
SAN FRANCISCO, CA 94123 USA
UK: Delphic HSE GU14 7NA
NL: 104 Schiphol, 1118CN
© 2024 TATCHA LLC

TATCHA.COM